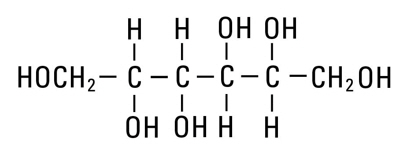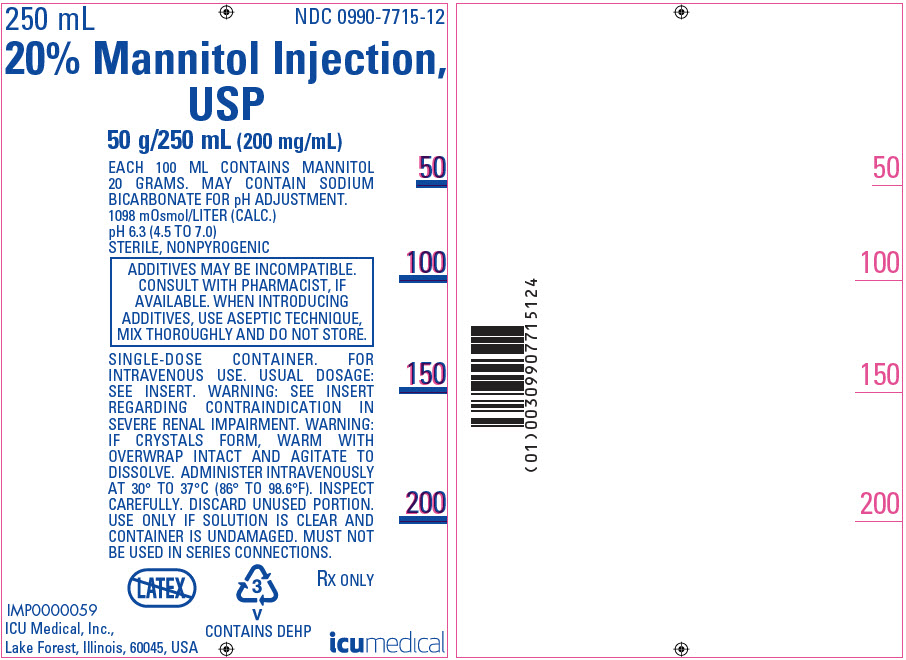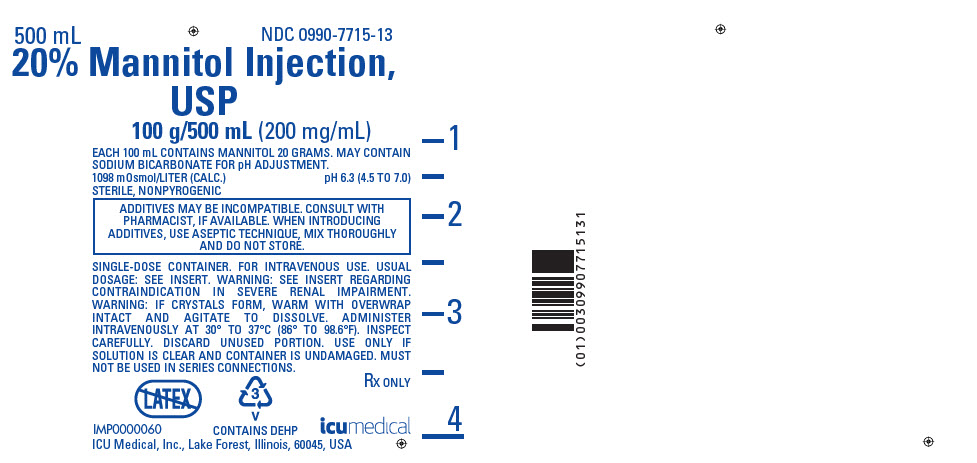 DRUG LABEL: Mannitol
NDC: 0990-7715 | Form: INJECTION, SOLUTION
Manufacturer: ICU Medical Inc.
Category: prescription | Type: HUMAN PRESCRIPTION DRUG LABEL
Date: 20251024

ACTIVE INGREDIENTS: MANNITOL 20 g/100 mL
INACTIVE INGREDIENTS: WATER; SODIUM BICARBONATE

HIGHLIGHTS OF PRESCRIBING INFORMATION

These highlights do not include all the information needed to use MANNITOL INJECTION safely and effectively. See full prescribing information for MANNITOL INJECTION.
MANNITOL injection, for intravenous use
Initial U.S. Approval: 1964

RECENT MAJOR CHANGES

Indications and Usage (removed, revised) (1) | 05/2020
Contraindications (4) | 05/2020
Warnings and Precautions (5.1, 5.2, 5.3, 5.4, 5.5, 5.6, 5.7) | 05/2020

1 INDICATIONS AND USAGE

Mannitol Injection is an osmotic diuretic indicated for the reduction of:

- intracranial pressure and treatment of cerebral edema. (1)
- elevated intraocular pressure. (1)

2 DOSAGE AND ADMINISTRATION

Administration Instructions (2.1):

- For intravenous infusion preferably into a large central vein.
- Prior to administration, evaluate renal, cardiac and pulmonary status, and correct fluid and electrolyte imbalances.

Recommended Dosage (2.2):

- The dosage, concentration and rate of administration depend on the age, weight and condition of the patient, including fluid requirement, urinary output and concomitant therapy.
- Reduction of Intracranial Pressure: 0.25 g/kg administered every 6 to 8 hours as an intravenous infusion over at least 30 minutes.
- Reduction of Intraocular Pressure: 1.5 to 2 g/kg as a single dose administered intravenously over at least 30 minutes. Administer 60 to 90 minutes before surgery to achieve maximal effect.

3 DOSAGE FORMS AND STRENGTHS

Injection: 20% (0.2 grams/mL); 20 grams of mannitol, USP per 100 mL in single-dose 250 mL and 500 mL flexible containers (3)

4 CONTRAINDICATIONS

- Known hypersensitivity to mannitol. (4, 5.1)
- Anuria. (4, 5.2)
- Severe hypovolemia. (4, 5.4)
- Pre-existing pulmonary vascular congestion or pulmonary edema. (4, 5.5)
- Active intracranial bleeding except during craniotomy. (4)

5 WARNINGS AND PRECAUTIONS

- Hypersensitivity Reactions, including anaphylaxis: Stop infusion immediately if hypersensitivity reactions develop. (5.1)
- Renal Complications Including Renal Failure: Risk factors include preexisting renal failure, concomitant use of nephrotoxic drugs or other diuretics. Avoid use of nephrotoxic drugs. Discontinue Mannitol Injection if renal function worsens. (5.2, 8.6)
- Central Nervous System (CNS) Toxicity: Confusion, lethargy and coma may occur during or after infusion. Concomitant neurotoxic drugs may potentiate toxicity. Avoid use of neurotoxic drugs. Discontinue Mannitol Injection if CNS toxicity develops. (5.3)
- Fluid and Electrolyte Imbalances, Hyperosmolarity: Hypervolemia may exacerbate congestive heart failure, hyponatremia can lead to encephalopathy; hypo/hyperkalemia can result in cardiac adverse reactions in sensitive patients. Discontinue Mannitol Injection if fluid and/or electrolyte imbalances occur. (5.4)
- Monitoring/Laboratory Tests: Monitor fluid and electrolytes, serum osmolarity and renal, cardiac and pulmonary function. Discontinue if toxicity develops. (5.5)
- Infusion Site Reactions: May include irritation and inflammation, as well as severe reactions (compartment syndrome) when associated with extravasation. (5.6)
- Interference with Laboratory Tests: High concentrations of mannitol may cause false low results of inorganic phosphorus blood concentrations. Mannitol may produce false positive results for blood ethylene glycol. (5.7, 7.6)

6 ADVERSE REACTIONS

The most common adverse reactions are hypersensitivity reactions, renal failure, CNS toxicity, hypo/hypervolemia, hypo/hypernatremia, hypo/hyperkalemia, and infusion site reactions. (6)

To report SUSPECTED ADVERSE REACTIONS, contact name ICU Medical, Inc. at 1-800-441-4100 or FDA at 1-800-FDA-1088 or www.fda.gov/medwatch.

7 DRUG INTERACTIONS

- Nephrotoxic Drugs and Diuretics: May increase the risk of renal failure; avoid concomitant use. (7.1, 7.2)
- Neurotoxic Drugs: May potentiate CNS toxicity of mannitol; avoid concomitant use. (7.3)
- Drugs Affected by Electrolyte Imbalances: May result in cardiac adverse reactions; monitor serum electrolytes and discontinue Mannitol Injection if cardiac status worsens. (7.4)
- Renally Eliminated Agents: Concomitant use may decrease the effectiveness of agents that undergo significant renal elimination. However, concomitant use of mannitol and lithium may increase risk of lithium toxicity. If concomitant use is necessary, frequently monitor lithium concentrations and for signs of toxicity. (7.5)

FULL PRESCRIBING INFORMATION

1 INDICATIONS AND USAGE

Mannitol Injection is indicated for the reduction of:

- intracranial pressure and treatment of cerebral edema;
- elevated intraocular pressure.

2 DOSAGE AND ADMINISTRATION

2.1 Important Preparation and Administration Instructions

- Mannitol Injection is for intravenous infusion preferably into a large central vein [see Warnings and Precautions (5.6), Description (11)].
- Prior to administration of Mannitol Injection, evaluate renal, cardiac, and pulmonary status of the patient and correct fluid and electrolyte imbalances [see Dosage and Administration (2.2)].
- Do not administer Mannitol Injection simultaneously with blood products through the same administration set because of the possibility of pseudoagglutination or hemolysis.

Preparation

1. Tear outer wrap at notch and remove solution container.
2. Visually inspect flexible container. Do not administer unless the solution is clear and the seal is intact.
  - If the outlet port protector is damaged, detached, or not present, discard container as solution path sterility may be impaired.
  - Some opacity of the plastic due to moisture absorption during the sterilization process may be observed. This is normal and does not affect the solution quality or safety. The opacity will diminish gradually.
3. Check for minute leaks prior to use by squeezing the bag firmly. If leaks are detected, discard solution as sterility may be impaired.
4. Admixing Mannitol Injection with other medications is not recommended.
5. Inspect Mannitol Injection visually for particulate matter and discoloration prior to administration. If particulates or discoloration are present, discard the bag.

Manitol Injection solutions may crystalize when exposed to low temperatures. Inspect Mannitol Injection for crystals prior to administration. If crystals are visible, re-dissolve by warming the solution up to 70°C with agitation. Heat solution by using a dry-heat cabinet with overwrap intact. The use of a water bath is not recommended. Allow the solution to cool to body temperature or less before administering. Reinspect Mannitol Injection for crystals prior to administration. Discard the solution if all the crystals cannot be dissolved.

Administration

1. Close flow control clamp of administration set.
2. Remove cover from outlet port at bottom of container.
3. Insert piercing pin of administration set into port with a twisting motion until the set is firmly seated. NOTE: See full directions on administration set carton.
4. Use administration sets with a final in-line filter because of the potential for mannitol crystals to form.
5. Suspend container from hanger.
6. Squeeze and release drip chamber to establish proper fluid level in chamber.
7. Open flow control clamp and clear air from set. Close clamp.
8. Attach set to venipuncture device. If device is not indwelling, prime and make venipuncture.
9. Regulate rate of administration with flow control clamp.
10. To prevent air embolism, use a non-vented infusion set or close the vent on a vented set, avoid multiple connections, do not connect flexible containers in series, fully evacuate residual gas in the container prior to administration, do not pressurize the flexible container to increase flow rates, and if administration is controlled by pumping device, turn off pump before the container runs dry.
11. For single use only; discard unused portion.

2.2 Recommended Dosage

Prior to administration of Mannitol Injection, evaluate renal, cardiac and pulmonary status of the patient and correct fluid and electrolyte imbalances.

The total dosage, concentration, and rate of administration depend on the age, weight, and condition of the patient being treated, including fluid requirement, electrolyte balance, serum osmolality, urinary output, and concomitant therapy.

The following outline of administration and dosage is only a general guide to therapy.

Reduction of Intracranial Pressure and Treatment of Cerebral Edema

Usually a maximum reduction in intracranial pressure can be achieved with a dose of 0.25 gram/kg given intravenously as an intravenous infusion over at least 30 minutes, which may be repeated every six to eight hours.

During and following Mannitol Injection infusion, monitor fluid and electrolytes, serum osmolarity, and renal, cardiac and pulmonary function. Discontinue Mannitol Injection if renal, cardiac, or pulmonary status worsens or CNS toxicity develops [see Warnings and Precautions (5.2, 5.3, 5.4, 5.5)].

Reduction of Intraocular Pressure

The recommended dosage is 1.5 to 2 g/kg as a single dose administered as an intravenous infusion over at least 30 minutes. When used preoperatively, administer Mannitol Injection 60 to 90 minutes before surgery to achieve maximal reduction of intraocular pressure before operation.

3 DOSAGE FORMS AND STRENGTHS

Injection: 20% (0.2 grams/mL); 20 grams of mannitol, USP per 100 mL as a clear and colorless solution in single-dose 250 mL and 500 mL flexible containers

4 CONTRAINDICATIONS

Mannitol Injection is contraindicated in patients with:

- Known hypersensitivity to mannitol [see Warnings and Precautions (5.1)]
- Anuria [see Warnings and Precautions (5.2)]
- Severe hypovolemia [see Warnings and Precautions (5.4)]
- Pre-existing pulmonary vascular congestion or pulmonary edema [see Warnings and Precautions (5.5)]
- Active intracranial bleeding except during craniotomy.

5 WARNINGS AND PRECAUTIONS

5.1 Hypersensitivity Reactions

Serious hypersensitivity reactions, including anaphylaxis, hypotension and dyspnea resulting in cardiac arrest and death have been reported with Mannitol Injection [see Adverse Reactions (6)].

Stop the infusion immediately if signs or symptoms of a suspected hypersensitivity reaction develop. Initiate appropriate therapeutic countermeasures as clinically indicated.

5.2 Renal Complications Including Renal Failure

Renal complications, including irreversible renal failure have been reported in patients receiving mannitol. Reversible, oliguric acute kidney injury has occurred in patients with normal pretreatment renal function who received large intravenous doses of mannitol. Although the osmotic nephrosis associated with mannitol administration is in principle reversible, osmotic nephrosis in general is known to potentially proceed chronic or even end-stage renal failure. Monitor renal function closely, including signs of urine output reduction, during Mannitol Injection infusion. Patients with pre-existing renal disease, patients with conditions that put them at high risk for renal failure, or those receiving potentially nephrotoxic drugs or other diuretics, are at increased risk of renal failure following administration of Mannitol Injection. Avoid concomitant administration of nephrotoxic drugs (e.g., aminoglycosides) or other diuretics with Mannitol Injection, if possible [see Drug Interactions (7.1, 7.2)].

Patients with oliguric acute kidney injury who subsequently develop anuria while receiving mannitol are at risk of congestive heart failure, pulmonary edema, hypertensive crisis, coma and death.

During and following Mannitol Injection infusion for the reduction in intracranial pressure, monitor the patient clinically and review laboratory tests for changes in fluid and electrolyte status. Discontinue Mannitol Injection if renal function worsens [see Warnings and Precautions (5.5)].

5.3 Central Nervous System (CNS) Toxicity

CNS toxicity manifested by, e.g., confusion, lethargy, coma has been reported in patients treated with mannitol, some resulting in death, in particular in the presence of impaired renal function CNS toxicity may result from high serum mannitol concentrations, serum hyperosmolarity resulting in intracellular dehydration within CNS, hyponatremia or other disturbances of electrolyte and acid/base balance secondary to mannitol administration [see Warnings and Precautions (5.4)].

At high concentrations, mannitol may cross the blood brain barrier and interfere with the ability of the brain to maintain the pH of the cerebrospinal fluid especially in the presence of acidosis.

In patients with preexisting compromise of the blood brain barrier, the risk of increasing cerebral edema (general and focal) associated with repeated or continued use of Mannitol Injection must be individually weighed against the expected benefits.

A rebound increase of intracranial pressure may occur several hours after the infusion. Patients with a compromised blood brain barrier are at increased risk.

Concomitant administration of neurotoxic drugs (e.g., aminoglycosides) with Mannitol Injection may potentiate neurotoxicity. Avoid concomitant use of neurotoxic drugs, if possible [see Drug Interactions (7.3)].

During and following Mannitol Injection infusion for the reduction in intracranial pressure, monitor the patient clinically and laboratory tests for changes in fluid and electrolyte status. Discontinue Mannitol Injection if CNS toxicity develops [see Warnings and Precautions (5.5)].

5.4 Fluid and Electrolyte Imbalances, Hyperosmolarity

Depending on dosage and duration, administration of Mannitol Injection may result in hypervolemia leading to or exacerbating existing congestive heart failure. Accumulation of mannitol due to insufficient renal excretion increases the risk of hypervolemia.

Mannitol-induced osmotic diuresis may cause or worsen dehydration/hypovolemia and hemoconcentration. Administration of Mannitol Injection may also cause hyperosmolarity [see Description (11)].

Depending on dosage and duration of administration, electrolyte and acid/base imbalances may also result from transcellular shifts in water and electrolytes, osmotic diuresis and/or other mechanisms. Such imbalances may be severe and potentially fatal.

Imbalances that may result from Mannitol Injection administration include:

- Hypernatremia, dehydration and hemoconcentration
- Hyponatremia, which can lead to headache, nausea, seizures, lethargy, coma, cerebral edema, and death. Acute symptomatic hyponatremic encephalopathy is considered a medical emergency.
- Hypo/hyperkalemia. The development of electrolyte imbalances (e.g., hyperkalemia, hypokalemia) associated with mannitol administration may result in cardiac adverse reactions in patients receiving drugs that are sensitive to such imbalances (e.g., digoxin, agents that may cause QT prolongation, neuromuscular blocking agents) [see Drug Interactions (7.4)].
- Other electrolyte disturbances
- Metabolic acidosis/alkalosis

Pediatric patients less than two years of age, particularly preterm and term neonates, may be at higher risk for fluid and electrolyte abnormalities following Mannitol Injection administration due to decreased glomerular filtration rate and limited ability to concentrate urine [see Use in Specific Populations (8.4)].

During and following Mannitol Injection infusion for the reduction in intracranial pressure, monitor fluid, acid-base balance and electrolyte status and discontinue Mannitol Injection if imbalances occur [see Warnings and Precautions (5.5)].

5.5 Monitoring/Laboratory Tests

During and following infusion of Mannitol Injection for reduction of intracranial pressure and monitor:

- serum osmolarity, serum electrolytes (sodium, potassium, calcium, and phosphate) and acid base balance
- the osmol gap
- signs and symptoms of hypo- or hypervolemia, including urine output
- renal, cardiac, and pulmonary function
- intracranial pressure

Discontinue Mannitol Injection if renal, cardiac, or pulmonary status worsens or CNS toxicity develops [see Contraindications (4)].

5.6 Infusion Site Reactions

The infusion of hypertonic solutions through a peripheral vein, including Mannitol Injection may result in peripheral venous irritation, including phlebitis. Other severe infusion site reactions, such as compartment syndrome and swelling associated with extravasation, can occur with administration of Mannitol Injection [see Adverse Reactions (6)]. Administration through a large central vein is preferred with mannitol [see Dosage and Administration (2.1)].

5.7 Interference with Laboratory Tests

High concentrations of mannitol can cause false low results for inorganic phosphorus blood concentrations [see Drug Interactions (7.6)].

Mannitol may produce false positive results in tests for blood ethylene glycol concentrations [see Drug Interactions (7.6)].

6 ADVERSE REACTIONS

The following adverse reactions from voluntary reports or clinical studies have been reported with Mannitol Injection. Because many of these reactions were reported voluntarily from a population of uncertain size, it is not always possible to reliably estimate their frequency or establish a causal relationship to drug exposure.

- Hypersensitivity reactions:, anaphylaxis, hypotension, dyspnea, hypertension, pyrexia, chills, sweating, urticaria/rash, pruritus [see Warnings and Precautions (5.1)]
- Renal Failure: acute kidney injury, osmotic nephrosis, azotemia, anuria, hematuria, oliguria, polyuria, urinary retention [see Warnings and Precautions (5.2)]
- CNS Toxicity: coma, seizures, confusion, lethargy; rebound increase in intracranial pressure; dizziness, headache [see Warnings and Precautions (5.3)]
- Fluid and Electrolyte Imbalances: hypovolemia (dehydration), hypervolemia, peripheral edema, , hyponatremia, hypernatremia, hyperkalemia, hypokalemia; metabolic acidosis [see Warning and Precautions (5.4)]
- Infusion Site Reactions: venous thrombosis, phlebitis, inflammation, pain, rash, erythema, pruritus; compartment syndrome and swelling associated with extravasation [see Warnings and Precautions (5.6)]
- Cardiac and Respiratory Disorders: cardiac arrest, congestive cardiac failure, pulmonary edema, palpitations, tachycardia, angina-like chest pain
- Musculoskeletal Disorders: musculoskeletal stiffness, myalgia
- Gastrointestinal Disorders: thirst, dry mouth, nausea, vomiting
- General Disorders: asthenia, malaise

7 DRUG INTERACTIONS

7.1 Nephrotoxic Drugs

Concomitant administration of nephrotoxic drugs (e.g., aminoglycosides, cyclosporine) increases the risk of renal failure following administration of mannitol. Avoid use of nephrotoxic drugs with Mannitol Injection, if possible [see Warnings and Precautions (5.2)].

7.2 Diuretics

Concomitant administration of other diuretics may potentiate the renal toxicity of mannitol. Avoid use of other diuretics with Mannitol Injection, if possible [see Warnings and Precautions (5.2)].

7.3 Neurotoxic Drugs

Concomitant administration of systemic neurotoxic drugs (e.g., aminoglycosides) with Mannitol Injection may potentiate the CNS toxicity of mannitol. Avoid concomitant administration of neurotoxic drugs with mannitol [see Warnings and Precautions (5.3)].

7.4 Drugs Affected by Electrolyte Imbalances

The development of electrolyte imbalances (e.g., hyperkalemia, hypokalemia) associated with mannitol administration may result in cardiac adverse reactions in patients receiving drugs that are sensitive to such imbalances (e.g., digoxin, drugs that prolong the QT interval, neuromuscular blocking agents) [see Warnings and Precautions (5.4)]. During and following Mannitol Injection infusion, monitor serum electrolytes and discontinue Mannitol Injection if cardiac status worsens [see Warnings and Precautions (5.5)].

7.5 Renally Eliminated Drugs

Mannitol may increase the elimination, and decrease the effectiveness of treatment with, drugs that undergo significant renal elimination. Concomitant administration of mannitol with lithium may initially increase the elimination of lithium but may also increase the risk of lithium toxicity in patients who develop hypovolemia or renal impairment. Consider holding lithium therapy during treatment with Mannitol Injection. If lithium therapy cannot be held, monitor serum lithium concentrations frequently for signs of lithium toxicity. Mannitol therapy may increase the elimination of digoxin leading to a potential decrease in effectiveness of the treatment. Monitor digoxin serum concentrations.

7.6 Interference with Laboratory Tests

High concentrations of mannitol can cause false low results for inorganic phosphorus blood concentrations when an assay based on the conversion of phosphate (orthophosphate) to the phosphomolybdate complex is used [see Warnings and Precautions (5.7)].

Mannitol may produce false positive results in tests for blood ethylene glycol concentrations in which mannitol is initially oxidized to an aldehyde [see Warnings and Precautions (5.7)].

8 USE IN SPECIFIC POPULATIONS

8.1 Pregnancy

Risk Summary

The available case report data with mannitol over decades of use have not identified a drug-associated risk of major birth defects, miscarriage or adverse maternal or fetal outcomes. Mannitol crosses the placenta and may cause fluid shifts that could potentially result in adverse effects in the fetus (see Data). No adverse developmental effects from mannitol were reported in published animal studies; however, fluid shifts occurred in fetal ewes in response to maternal infusion of mannitol.

The estimated background risk of major birth defects and miscarriage for the indicated population is unknown. All pregnancies have a background risk of birth defect, loss, or other adverse outcomes. In the U.S. general population, the estimated background risk of major birth defects and miscarriage in clinically recognized pregnancies is 2 to 4% and 15 to 20%, respectively.

Data

Human Data

Published literature reports the presence of mannitol in amniotic fluid when mannitol is administered to pregnant women during the third trimester of pregnancy.

8.2 Lactation

Risk Summary

There are no data on the presence of mannitol in either human or animal milk, the effects on the breastfed infant, or the effects on milk production. The developmental and health benefits of breastfeeding should be considered along with the mother's clinical need for Mannitol Injection and any potential adverse effects on the breastfed infant from Injection or from the underlying maternal condition.

8.4 Pediatric Use

Mannitol Injection is approved for use in the pediatric population for the reduction of intracranial and intraocular pressure. Studies have not defined the optimal dose of Mannitol Injection in the pediatric population. The safety profile for mannitol use in pediatric patients is similar to adults at dosages described in labeling. However, pediatric patients less than two years of age, particularly preterm and term neonates, may be at higher risk for fluid and electrolyte abnormalities following Mannitol Injection administration due to decreased glomerular filtration rate and limited ability to concentrate urine [see Warnings and Precautions (5.4)].

8.5 Geriatric Use

Mannitol is known to be substantially excreted by the kidney and the risk of adverse reactions to this drug may be greater in elderly patients with impaired renal function. Evaluate the renal, cardiac, and pulmonary status of the patient and correct fluid and electrolyte imbalances prior to administration of Mannitol Injection [see Warnings and Precautions (5.2, 5.3, 5.4, 5.5)].

8.6 Renal Impairment

Patients with pre-existing renal disease, patients with conditions that put them at high risk of renal failure, or those receiving potentially nephrotoxic drugs or other diuretics, are at increased risk of renal failure with administration of mannitol. Evaluate the renal, cardiac, and pulmonary status of the patient and correct fluid and electrolyte imbalances prior to administration of Mannitol Injection [see Warnings and Precautions (5.2, 5.3, 5.4, 5.5)].

10 OVERDOSAGE

Signs and symptoms of overdose with Mannitol Injection include renal failure and acute kidney injury, hypo/hypervolemia, hyperosmolarity and electrolyte imbalances, CNS toxicity (e.g., coma, seizures), some of which can be fatal [see Warnings and Precautions (5.2, 5.3, 5.4)].

Management of overdosage with Mannitol Injection is symptomatic and supportive. Discontinue the infusion and institute appropriate corrective measures with particular attention to renal, cardiac and pulmonary systems. Correct fluid and electrolyte imbalances.

Mannitol Injection is dialyzable (hemodialysis and peritoneal dialysis), hemodialysis may increase Mannitol Injection elimination.

11 DESCRIPTION

Mannitol Injection, USP is a sterile, nonpyrogenic solution of mannitol in water for injection available in a concentration of 20% in flexible plastic containers.

The content and characteristics of the available concentration is as follows:

Concentration (%) | g/100 mL | mOsmol/liter (calc.) | pH [may contain sodium bicarbonate for pH adjustment.]
20 | 20 | 1098 | 6.3 (4.5 to 7.0)

The solution contains no bacteriostat, antimicrobial agent or added buffer (except for pH adjustment) and is intended only as a single-dose injection. When smaller doses are required the unused portion should be discarded.

Mannitol Injection, USP is an osmotic diuretic for intravenous administration.

Mannitol, USP is chemically designated D-mannitol (C6H14O6), a white crystalline powder or free-flowing granules freely soluble in water. It has the following structural formula:

Water for Injection, USP is chemically designated H2O.

The flexible plastic container is fabricated from a specially formulated polyvinylchloride. Water can permeate from inside the container into the overwrap, but not in amounts sufficient to affect the solution significantly. Solutions in contact with the plastic container may leach out certain chemical components from the plastic in very small amounts; however, biological testing was supportive of the safety of the plastic container materials. Exposure to temperatures above 25°C/77°F during transport and storage will lead to minor losses in moisture content. Higher temperatures lead to greater losses. It is unlikely that these minor losses will lead to clinically significant changes within the expiration period.

12 CLINICAL PHARMACOLOGY

12.1 Mechanism of Action

Mannitol, when administered intravenously, exerts its osmotic diuretic effect as a solute of relatively small molecular size being largely confined to the extracellular space. Mannitol hinders tubular reabsorption of water and enhances excretion of sodium and chloride by elevating the osmolarity of the glomerular filtrate.

This increase in extracellular osmolarity affected by the intravenous administration of mannitol will induce the movement of intracellular water to the extracellular and vascular spaces. This action underlies the role of mannitol in reducing intracranial pressure, intracranial edema, and intraocular pressure.

12.3 Pharmacokinetics

Distribution

Mannitol distributes largely in the extracellular space in 20 to 40 minutes after intravenous administration. The volume of distribution of mannitol is approximately 17 L in adults.

Elimination

In subjects with normal renal function, the total clearance is 87 to 109 mL/min. The elimination half-life of mannitol is 0.5 to 2.5 hours.

Metabolism

Only relatively small amount of the dose administered is metabolized after intravenous administration of mannitol to healthy subjects.

Excretion

Mannitol is eliminated primarily via the kidneys in unchanged form. Mannitol is filtered by the glomeruli, exhibits less than 10% of tubular reabsorption, and is not secreted by tubular cells. Following intravenous administration, approximately 80% of an administered dose of mannitol is estimated to be excreted in the urine in three hours with lesser amounts thereafter.

Specific Populations

Patients with Renal Impairment

In patients with renal impairment, the elimination half-life of mannitol is prolonged. In a published study, in patients with renal impairment including acute renal failure and end stage renal failure, the elimination half-life of mannitol was estimated at about 36 hours, based on serum osmolarity. In patients with renal impairment on dialysis, the elimination half-life of mannitol was reduced to 6 and 21 hours during hemodialysis and peritoneal dialysis, respectively. [see Use in Specific Populations (8.6), Overdosage (10)].

16 HOW SUPPLIED/STORAGE AND HANDLING

Mannitol Injection is a clear and colorless solution supplied in single-dose containers as follows:

Unit of Sale | Concentration | Each
NDC 0409-7715-03 NDC 0990-7715-03 Case containing 12 | 20% (0.2 g/mL) mannitol, USP | NDC 0409-7715-13 NDC 0990-7715-13 500 mL Flexible Container
NDC 0409-7715-02 NDC 0990-7715-02 Case containing 24 | 20% (0.2 g/mL) mannitol, USP | NDC 0409-7715-12 NDC 0990-7715-12 250 mL Flexible Container
ICU Medical is transitioning NDC codes from "0409" to "0990" labeler code. Both NDC codes are expected to be in the market for a period of time.

STORAGE AND HANDLING

Protect from freezing. Store at 20 to 25°C (68 to 77°F). [See USP Controlled Room Temperature.]

17 PATIENT COUNSELING INFORMATION

Inform patients, caregivers, or home healthcare providers of the following risks of Mannitol Injection:

- Hypersensitivity Reactions [see Warnings and Precautions (5.1)]
- Renal Failure [see Warnings and Precautions (5.2)]
- CNS Toxicity [see Warnings and Precautions (5.3)]
- Fluid and Electrolyte Imbalances, Hyperosmolarity [see Warnings and Precautions (5.4)]
- Infusion Site Reactions [see Warnings and Precautions (5.6)]

EN-4730

Manufactured by:
ICU Medical, Inc., Lake Forest, Illinois, 60045 USA

PRINCIPAL DISPLAY PANEL - 250 mL Bag Label

250 mL
NDC 0990-7715-12

20% Mannitol Injection,
USP

50 g/250 mL (200 mg/mL)

EACH 100 ML CONTAINS MANNITOL
20 GRAMS. MAY CONTAIN SODIUM
BICARBONATE FOR pH ADJUSTMENT.
1098 mOsmol/LITER (CALC.)
pH 6.3 (4.5 TO 7.0)
STERILE, NONPYROGENIC

ADDITIVES MAY BE INCOMPATIBLE.
CONSULT WITH PHARMACIST, IF
AVAILABLE. WHEN INTRODUCING
ADDITIVES, USE ASEPTIC TECHNIQUE,
MIX THOROUGHLY AND DO NOT STORE.

SINGLE-DOSE CONTAINER. FOR
INTRAVENOUS USE. USUAL DOSAGE:
SEE INSERT. WARNING: SEE INSERT
REGARDING CONTRAINDICATION IN
SEVERE RENAL IMPAIRMENT. WARNING:
IF CRYSTALS FORM, WARM WITH
OVERWRAP INTACT AND AGITATE TO
DISSOLVE. ADMINISTER INTRAVENOUSLY
AT 30° TO 37°C (86° TO 98.6°F). INSPECT
CAREFULLY. DISCARD UNUSED PORTION.
USE ONLY IF SOLUTION IS CLEAR AND
CONTAINER IS UNDAMAGED. MUST NOT
BE USED IN SERIES CONNECTIONS.

3
V
CONTAINS DEHP

Rx ONLY

IMP0000059
ICU Medical, Inc.,
Lake Forest, Illinois, 60045, USA

icumedical

PRINCIPAL DISPLAY PANEL - 500 mL Bag Label

500 mL
NDC 0990-7715-13

20% Mannitol Injection,
USP

100 g/500 mL (200 mg/mL)

EACH 100 mL CONTAINS MANNITOL 20 GRAMS. MAY CONTAIN
SODIUM BICARBONATE FOR pH ADJUSTMENT.
1098 mOsmol/LITER (CALC.)
pH 6.3 (4.5 TO 7.0)
STERILE, NONPYROGENIC

ADDITIVES MAY BE INCOMPATIBLE. CONSULT WITH
PHARMACIST, IF AVAILABLE. WHEN INTRODUCING
ADDITIVES, USE ASEPTIC TECHNIQUE, MIX THOROUGHLY
AND DO NOT STORE.

SINGLE-DOSE CONTAINER. FOR INTRAVENOUS USE. USUAL
DOSAGE: SEE INSERT. WARNING: SEE INSERT REGARDING
CONTRAINDICATION IN SEVERE RENAL IMPAIRMENT.
WARNING: IF CRYSTALS FORM, WARM WITH OVERWRAP
INTACT AND AGITATE TO DISSOLVE. ADMINISTER
INTRAVENOUSLY AT 30° TO 37°C (86° TO 98.6°F). INSPECT
CAREFULLY. DISCARD UNUSED PORTION. USE ONLY IF
SOLUTION IS CLEAR AND CONTAINER IS UNDAMAGED. MUST
NOT BE USED IN SERIES CONNECTIONS.

3
V
CONTAINS DEHP

Rx ONLY

IMP0000060
ICU Medical, Inc., Lake Forest, Illinois, 60045, USA

icumedical